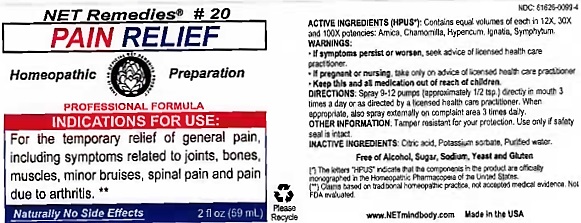 DRUG LABEL: PAIN RELIEF
NDC: 61626-0099 | Form: LIQUID
Manufacturer: NET Remedies
Category: homeopathic | Type: HUMAN PRESCRIPTION DRUG LABEL
Date: 20210119

ACTIVE INGREDIENTS: ARNICA MONTANA 12 [hp_X]/59 mL; MATRICARIA CHAMOMILLA 12 [hp_X]/59 mL; HYPERICUM PERFORATUM 12 [hp_X]/59 mL; STRYCHNOS IGNATII SEED 12 [hp_X]/59 mL; COMFREY ROOT 12 [hp_X]/59 mL
INACTIVE INGREDIENTS: CITRIC ACID MONOHYDRATE; POTASSIUM SORBATE; WATER

PAIN RELIEF

ACTIVE INGREDIENT

ACTIVE INGREDIENTS (HPUS*): Contains equal volumes of each in 12X, 30X, and 100X potencies: Arnica, Chamomilla, Hypericum, Ignatia, Symphytum.

(*) The letters "HPUS" indicate that the components in the product are officially monographed in the Homeopathic Pharmacopeia of the United States.

(**) Claims based on traditional homeopathic practice, not accepted medical evidence. Not FDA evaluated.

INDICATIONS AND USAGE

INDICATIONS FOR USE: For the temporary relief of general pain, includingm symptoms related to joints, bones, muscles, minor bruises, spinal pain and pain due to arthiritis. **

WARNINGS:

• If symptoms persist or worsen, seek advice of licensed health care practitioner.

• If pregnant or nursing, take on only advice of licensed health care practitioner.

• Keep this and all medication out of reach of children.

KEEP OUT OF REACH OF CHILDREN

• Keep this and all medication out of reach of children.

DOSAGE AND ADMINISTRATION

DIRECTIONS: Spray 9-12 pumps (approximately 1/2 tsp.) directly in mouth 3 times a day or as directed by a licensed health care practitioner. When appropriate, also spray externally on complaint area 3 times daily.

OTHER INFORMATION: Tamper resistant for your protection. Use only if safety seal is intact.

INACTIVE INGREDIENTS: Citric acid, Potassium sorbate, Purified water.

Free of Alcohol, Sugar, Sodium, Yeast and Gluten

QUESTIONS

www.NETmindbody.com

Made in the USA

PACKAGE LABEL

NET Remedies #20

PAIN RELIEF

Homeopathic Preparation

PROFESSIONAL FORMULA

Naturally No Side Effects

2 fl oz (59 mL)

PURPOSE

INDICATIONS FOR USE: For the temporary relief of general pain, includingm symptoms related to joints, bones, muscles, minor bruises, spinal pain and pain due to arthiritis. **